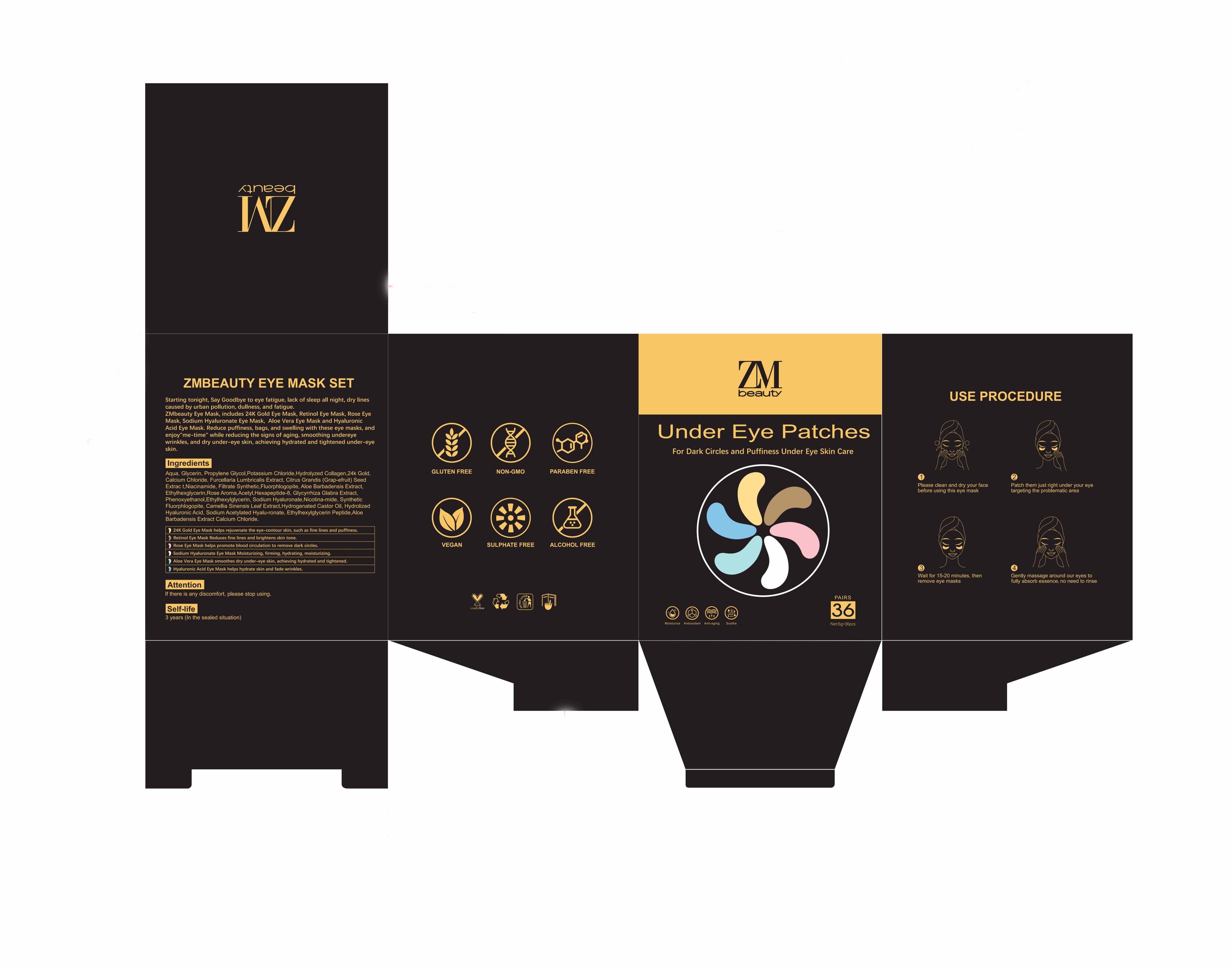 DRUG LABEL: Under Eye Patches
NDC: 84716-778 | Form: DRESSING
Manufacturer: Shenzhen Boyang E-commerce Co.
Category: otc | Type: HUMAN OTC DRUG LABEL
Date: 20240927

ACTIVE INGREDIENTS: GOLD 0.1512 g/216 g; GLYCERIN 21.6 g/216 g
INACTIVE INGREDIENTS: POTASSIUM CHLORIDE 6.48 g/216 g

ACTIVE INGREDIENT

GLYCERIN 10%
POTASSIUM CHLORIDE 3%
GOLD 0.07%

Purpose

Starting tonight, Say Goodbye to eye fatigue, lack of sleep all night, dry lines caused by urban pollution, dullness, and fatigue.ZMbeauty Eye Mask, includes 24K Gold Eye Mask, Retinol Eye Mask, Rose Eye Mask, Sodium Hyaluronate Eye Mask, Aloe Vera Eye Mask and Hyaluronic Acid Eye Mask, Reduce puffiness, bags, and swelling with these eye masks, and enjoy"me-time" while reducing the signs of aging, smoothing undereye wrinkles, and dry under-eye skin, achieving hydrated and tightened under-eye skin.

DOSAGE AND ADMINISTRATION

Please clean and dry your facebefore using this eye mask;
Patch them just right under your eye targeting the problematic area;

Wait for 15-20 minutes, then remove eye masks;
Gently massage around our eyes to fully absorb essence, no need to rinse.

USE 2-3 TIMES A WEEK FOR OPTIMAL AND LASTING RESULTS.DNE TIME USE, DISCARD AFTER USING.

WARNING: FOR EXTERNAL USE ONLY, DO NOT INGEST. KEEP OUT OF REACH OF CHILDREN.

USES

1.Please clean and dry your face before using this eye mask

2.Patch them just right under your eye targeting the problematic area

3.Wait for 15-20 minutes, then remove eye masks
4.Gently massage around our eyes to fully absorb essence, no need to rinse

WARNING

FOR EXTERNAL USE ONLY,

DO NOT INGEST.

KEEP OUT OF REACHCF CHILDREN.

If there is any discomfort, please stop using.

Keep out of reach of children.

If swallowed, get medical help or contact a Poison Control Center right away

INACTIVE INGREDIENT

WATER，GOLD，FRAGRANCE，SYNTHETIC FLUORPHLOGOPITE，HYDROGENATED CASTOR OIL